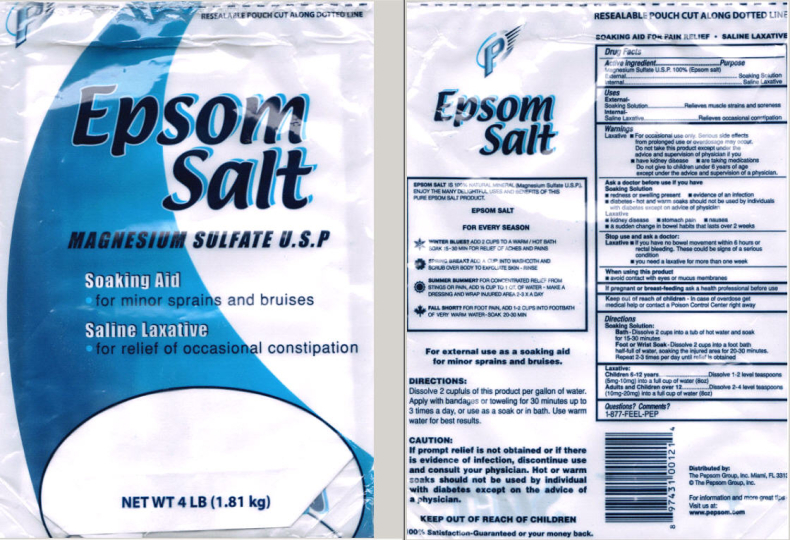 DRUG LABEL: PEPSOM FLYING P EPSOM SALT 
NDC: 51619-600 | Form: FOR SOLUTION
Manufacturer: The Pepsom Group, Inc.
Category: otc | Type: HUMAN OTC DRUG LABEL
Date: 20100526

ACTIVE INGREDIENTS: Magnesium Sulfate, Unspecified 1 kg/1 kg

Flying P Epsom Salt
Drug Facts

Active Ingredient

Magnesium Sulfate U.S.P. 100% (Epsom salt)

PURPOSE

External...................Soaking Solution
Internal.......................Saline Laxative

Uses

External-
Soaking Solution.............Relieves muscle strains and soreness
Internal-
Saline Laxative........................Relieves occasional constipation

Warnings

Laxative

- For occasional use only. Serious side effects from prolonged use or overdosage may occur. Do not take this product except under the advice and supervision of physician if you
  - have kidney disease
  - are taking medications
  Do not give to children under 6 years of age except under the advice and supervision of a physician.

Ask a doctor before use if you have

Soaking Solution

- redness or swelling present
- evidence of an infection
- diabetes - hot and warm soaks should not be used by individuals with diabetes except on advice of physician

Laxative

- kidney disease
- stomach pain
- nausea
- a sudden change in bowel habits that lasts over 2 weeks

Stop use and ask a doctor:

Laxative

- if you have no bowel movement within 6 hours or rectal bleeding. These could be signs of a serious condition
  - you need a laxative for more than one week

When using this product

- avoid contact with eyes or mucus membranes

PREGNANCY OR BREAST FEEDING

If pregnant or breast-feeding ask a health professional before use

Keep out of reach of children -

In case of overdose get medical help or contact a Poison Control Center right away

Directions

Soaking Solution:

Bath - Dissolve 2 cups into a tub of hot water and soak for 15-30 minutes
Foot or Wrist Soak - Dissolve 2 cups into a foot bath half-full of water, soaking the injured area for 20-30 minutes. Repeat 2-3 times per day until relief is obtained

Laxative:

Children 6-12 years.........................Dissolve 1-2 level teaspoons
(5mg-10mg) into a full cup of water (8oz)
Adults and Children over 12.........Dissolve 2-4 level teaspoons
(10mg-20mg) into a full cup of water (8oz)

INACTIVE INGREDIENTS

None

Questions? Comments?

1-877-FEEL-PEP

Principal Display Panel

RESEALABLE POUCH CUT ALONG DOTTED LINE

Epsom Salt

MAGNESIUM SULFATE U.S.P.

Soaking Aid

- for minor sprains and bruises

Saline Laxative

- for relief of occasional constipation

NET WT 4 LB (1.81 kg)

RESEALABLE POUCH CUT ALONG DOTTED LINE

EPSOM SALT IS 100% NATURAL MINERAL (Magnesium Sulfate U.S.P.).
ENJOY THE MANY DELIGHTFUL USES AND BENEFITS OF THIS
PURE EPSOM SALT PRODUCT.

EPSOM SALT

FOR EVERY SEASON

WINTER BLUES? ADD 2 CUPS TO A WARM/HOT BATH SOAK 15-30 MIN FOR RELIEF OF ACHES AND PAINS

SPRING BREAK? ADD A CUP INTO WASHCLOTH AND SCRUB OVER BODY TO EXFOLIATE SKIN - RINSE

SUMMER BUMMER? FOR CONCENTRATED RELIEF FROM STINGS OR PAIN, ADD 1/2 CUP TO 1 QT. OF WATER - MAKE A DRESSING AND WRAP INJURED AREA 2-3 X A DAY

FALL SHORT? FOR FOOT PAIN, ADD 1-2 CUPS INTO FOOTBATH OF VERY WARM WATER - SOAK 20-30 MIN

For external use as a soaking aid for minor sprains and bruises.

DIRECTIONS:
Dissolve 2 cupfuls of this product per gallon of water. Apply with bandages or toweling for 30 minutes up to 3 times a day, or use as a soak or in bath. Use warm water for best results.

CAUTION:
If prompt relief is not obtained or if there is evidence of infection, discontinue use and consult your physician. Hot or warm soaks should not be used by individual with diabetes except on the advice of a physician.

KEEP OUT OF REACH OF CHILDREN

100% Satisfaction-Guaranteed or your money back.

Distributed by:
The Pepsom Group, Inc. Miami, FL 33137
© The Pepsom Group, Inc.

For information and more great tips
Visit us at:
www.pepsom.com